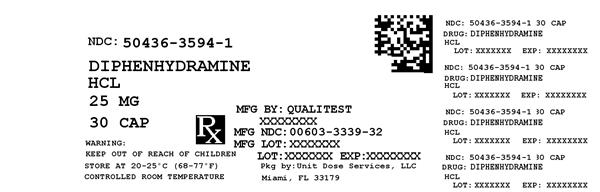 DRUG LABEL: Diphenhydramine Hydrochloride
                                    
NDC: 50436-3594 | Form: CAPSULE
Manufacturer: Unit Dose Services
Category: otc | Type: HUMAN OTC DRUG LABEL
Date: 20121120

ACTIVE INGREDIENTS: DIPHENHYDRAMINE HYDROCHLORIDE 25 mg/1 1
INACTIVE INGREDIENTS: BENZYL ALCOHOL; BUTYLPARABEN; D&C RED NO. 28; FD&C BLUE NO. 1; FD&C RED NO. 40; GELATIN; LACTOSE; MAGNESIUM STEARATE; METHYLPARABEN; POLYSORBATE 80; PROPYLPARABEN; SODIUM LAURYL SULFATE

DIPHENHYDRAMINE HYDROCHLORIDE CAPSULES, USP 25mg

Drug Facts

.

Active Ingredient

(in each capsule)

Diphenhydramine HCl 25 mg

Purpose

Antihistamine

Uses

temporarily relieves these symptoms of hay fever or other upper respiratory allergies:

- runny nose
- itchy nose or throat
- sneezing
- itchy, watery eyes

WARNINGS

with any other product containing diphenhydramine, even one used on skin Do not use

Ask a doctor before use if you have

- glaucoma
- trouble urinating due to an enlarged prostate gland
- a breathing problem such as emphysema or chronic bronchitis
  taking sedatives or tranquilizers Ask a doctor or pharmacist before use if you are
  When using this product
- you may get very drowsy
- avoid alcoholic drinks
- alcohol, sedatives & tranquilizers may increase drowsiness
- be careful when driving a motor vehicle or operating machinery
- excitability may occur, especially in children
  ask a health professional before use. If pregnant or breast-feeding,

Keep out of reach of children.

In case of overdose, get medical help or contact a Poison Control Center right away.

Directions

- take 1 to 2 capsules every 4-6 hours; not more than 6 doses in 24 hours adults and children 12 years and over:
- ask a doctor children under 12 years:

Other Information

- store at 15-30 °C (59-86 °F)
- protect from moisture
- For 1000 Count: This is a bulk package. Dispense contents in a tight, light-resistant container with a child-resistant closure as defined in the USP

Inactive Ingredients

benzyl alcohol, butylparaben, D&C red# 28, edible black ink, FD&C bule #1, FD&C red# 40, gelatin, lactose, magnesium stearate, methylparaben, polysorbate 80, propylparaben, sodium laurel sulfate

Questions or Comments

TAMPER EVIDENT: DO NOT USE IF IMPRINTED SAFETY SEAL UNDER CAP OR BAND AROUND ANY CAPSULE IS MISSING OR DAMAGED

Distributed by: Qualitest Pharmaceuticals, Inc.